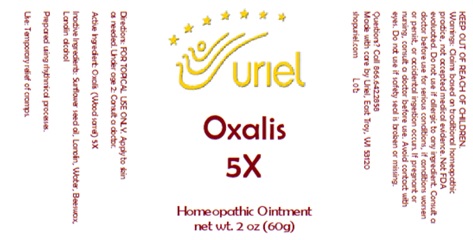 DRUG LABEL: Oxalis 5X
NDC: 48951-7224 | Form: OINTMENT
Manufacturer: Uriel Pharmacy, Inc
Category: homeopathic | Type: HUMAN OTC DRUG LABEL
Date: 20260202

ACTIVE INGREDIENTS: OXALIS STRICTA WHOLE 5 [hp_X]/1 g
INACTIVE INGREDIENTS: LANOLIN ALCOHOL; WATER; LANOLIN; BEESWAX; SUNFLOWER OIL

Oxalis 5X

INDICATIONS AND USAGE

Directions: FOR TOPICAL USE ONLY.

DOSAGE AND ADMINISTRATION

Apply to skin as needed. Under age 2: Consult a doctor.

Active Ingredient: Oxalis (Wood sorrel) 5X

INACTIVE INGREDIENT

Inactive Ingredients: Sunflower seed oil, Lanolin, Water, Beeswax, Lanolin alcohol

Prepared using rhythmical processes.

PURPOSE

Use: Temporary relief of cramps.

KEEP OUT OF REACH OF CHILDREN.

WARNINGS

Warnings: Claims based on traditional homeopathic practice, not accepted medical evidence. Not FDA evaluated. Do not use if allergic to any ingredient. Consult a doctor before use for serious conditions, if conditions worsen or persist, or accidental ingestion occurs. If pregnant or nursing, consult a doctor before use. Avoid contact with eyes. Do not use if safety seal is broken or missing.

Questions? Call 866.642.2858
Made with care by Uriel, East Troy, WI 53120
shopuriel.com Lot: